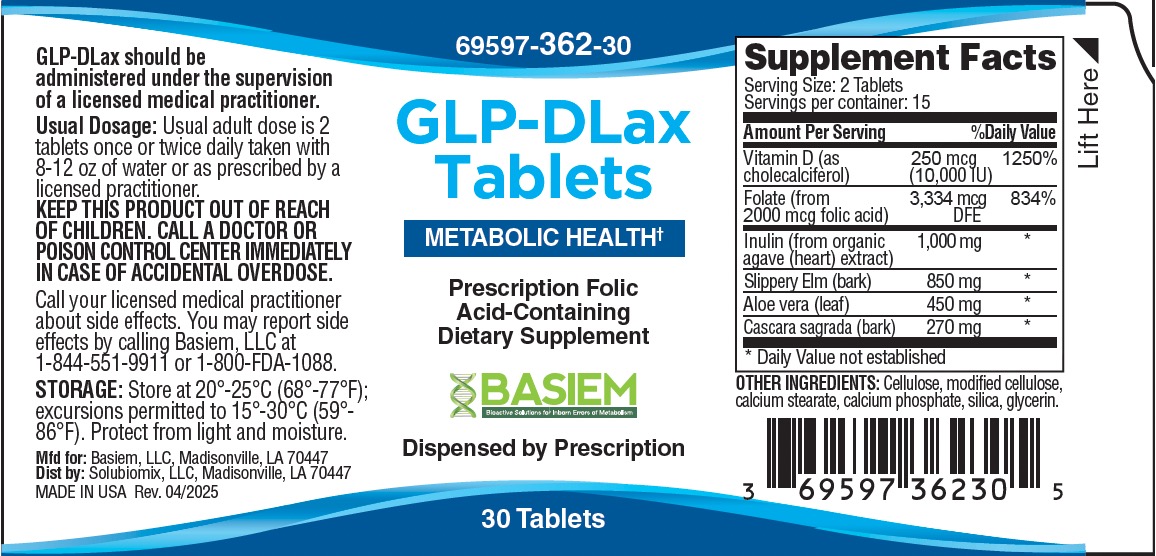 DRUG LABEL: GLP DLax
NDC: 69597-362 | Form: TABLET
Manufacturer: Basiem, LLC
Category: other | Type: DIETARY SUPPLEMENT
Date: 20250616

ACTIVE INGREDIENTS: BLUE AGAVE INULIN (AGAVE TEQUILANA) 500 mg/1 1; ELM 425 mg/1 1; ALOE FEROX LEAF 225 mg/1 1; RHAMNUS CATHARTICA BARK 135 mg/1 1; FOLIC ACID 1 mg/1 1; CHOLECALCIFEROL .125 mg/1 1
INACTIVE INGREDIENTS: CELLULOSE ACETATE; CALCIUM STEARATE; CALCIUM PHOSPHATE; SILICA

GLP-DLax Tablets

STATEMENT OF IDENTITY

GLP-DLax Tablets 69597-362-30*

Dietary Supplemement

Dispensed by Prescription†

Amount Per Serving (2 tablets): |  | %DV
Vitamin D (as cholecalciferol) | 250 mcg; (10,000 IU) | 1250%
Folate (from 2,000 mcg Folic Acid) | 3,334 mcg; DFE | 834%
Inulin (from organic agave (heart) extract) 1,000 mg *
Slippery Elm (bark) 850 mg *
Aloe Vera (leaf) 450 mg *
Cascara sagrada (bark) 270 mg *
*Daily Values (DV) not established

OTHER INGREDIENTS: Cellulose, calcium stearate, calcium phosphate, silica

GLP-DLax capsules are an orally administered prescription vitamin formulation for the clinical dietary management of suboptimal nutritional status in patients where advanced supplementation is required and for patients with occasional constipation to restore and maintain regularity.
These statements have not been evaluated by the Food and Drug Administration. This product is not intended to diagnose, treat, cure or prevent disease.

GLP-DLax is manufactured in accordance with Current Good Manufacturing Practice for foods, using ingredients that have been approved by the U.S. Food and Drug Administration (FDA) as food additives or are “Generally Recognized as Safe” (GRAS) for their intended use.

DOSAGE

Take two tablets once or twice daily with 8-12 oz of water or as directed by a healthcare practitioner.

SAFE HANDLING

CONTRAINDICATIONS
This product is contraindicated in patients with a known hypersensitivity to any of the ingredients. GLP-DLax is contraindicated in patients with hypercalcemia, malabsorption syndrome, abnormal sensitivity to the toxic effects of vitamin D, and hypervitaminosis D.

WARNINGS AND PRECAUTIONS
Tell your doctor if you have kidney problems or thyroid disease. Do not use this product if you have abdominal pain, diarrhea, or loose stools. Rectal bleeding and/or failure to have a bowel movement after the use of a laxative formula may be an indication of a more serious condition. Should this occur, or if you have a known medical condition and are taking this medication, consult your healthcare provider about the risks and benefits prior to taking this or any dietary supplement.

Folic acid alone is improper therapy in the treatment of pernicious anemia and other megaloblastic anemias where vitamin B12 is deficient. Folic acid in doses above 0.1 mg daily may obscure pernicious anemia in that hematologic remission can occur while neurological manifestations progress.

ADVERSE REACTIONS
Allergic sensitization has been reported following both oral and parenteral administration of folic acid.
You should call your doctor for medical advice about serious adverse events. To report adverse side effects or to obtain product information, contact Basiem, LLC, at 1-844-551-9911.

KEEP OUT OF REACH OF CHILDREN

STORAGE

Store at 20°-25°C (68°-77°F); excursions permitted to 15°-30°C (59°-86°F) [See USP Controlled Room Temperature.]

HOW SUPPLIED HEALTH CLAIM

GLP-DLax, Metabolic Support

Dietary Supplement

Vegan tablets are light brown and have an oval shape

Bottles contain 30 Tablets 69597-362-30*

Manufactured in USA for:
Basiem, LLC

Madisonville, LA 70447

Rev. 05/2025

*Basiem does not represent these product codes to be National Drug Codes (NDC). Product codes are formatted according to standard industry practice, to meet the formatting requirement by pedigree reporting and supply-chain control including pharmacies.

Dispensed by Prescription†All prescriptions using this product shall be pursuant to state statutes as applicable. This is not an Orange Book product. This product may be administered only under a physician’s supervision.

This product is a prescription-folate with or without other dietary ingredients that – due to increased folate levels increased risk associated with masking of B12 deficiency (pernicious anemia) requires administration under the care of a licensed medical practitioner (61 FR 8760).1-3 The most appropriate way to ensure pedigree reporting consistent with these regulatory guidelines and safety monitoring is to dispense this product only by prescription (Rx). This is not an Orange Book product. This product may be administered only under a physician’s supervision and all prescriptions using this product shall be pursuant to state statutes as applicable. The ingredients, indication or claims of this product are not to be construed to be drug claims.

1. Federal Register Notice of August 2, 1973 (38 FR 20750)
2. Federal Register Notice of October 17, 1980 (45 FR 69043, 69044)
3. Federal Register Notice of March 5, 1996 (61 FR 8760)

GLP-DLAX LABEL:

Label: